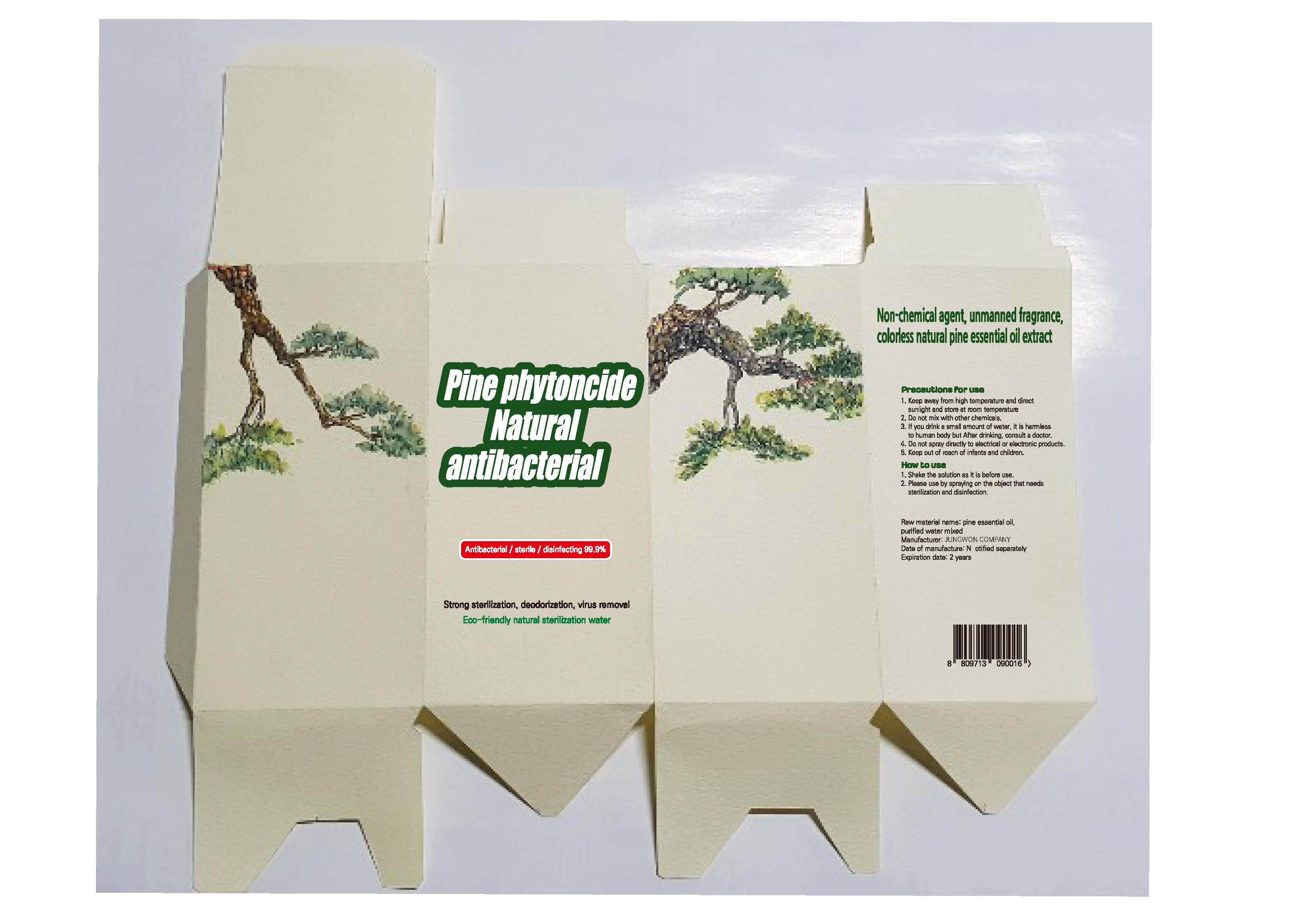 DRUG LABEL: Pine Phytoncide Antiseptic Solution
NDC: 74340-0001 | Form: LIQUID
Manufacturer: Jungwon Company
Category: otc | Type: HUMAN OTC DRUG LABEL
Date: 20200428

ACTIVE INGREDIENTS: PINUS DENSIFLORA WHOLE 20 g/100 mL
INACTIVE INGREDIENTS: WATER

Drug Facts

ACTIVE INGREDIENT

Pinus Densiflora Extract

INACTIVE INGREDIENT

Water

PURPOSE

antibiosis

KEEP OUT OF REACH OF THE CHILDREN

INDICATIONS AND USAGE

Store under 30°C (86°F)

WARNINGS

For external use only.

Flammable, keep away from fire or flame.

When using this product keep out of eyes. If contact with eyes occurs, rinse promptly and thoroughly with water.

Stop use and ask a doctor if significant irritation or sensitization develops.

Keep out of reach of children. If swallowed, get medical help or contact a Poison Control Center right away.

DOSAGE AND ADMINISTRATION

Spray well using on objects for sterilization.